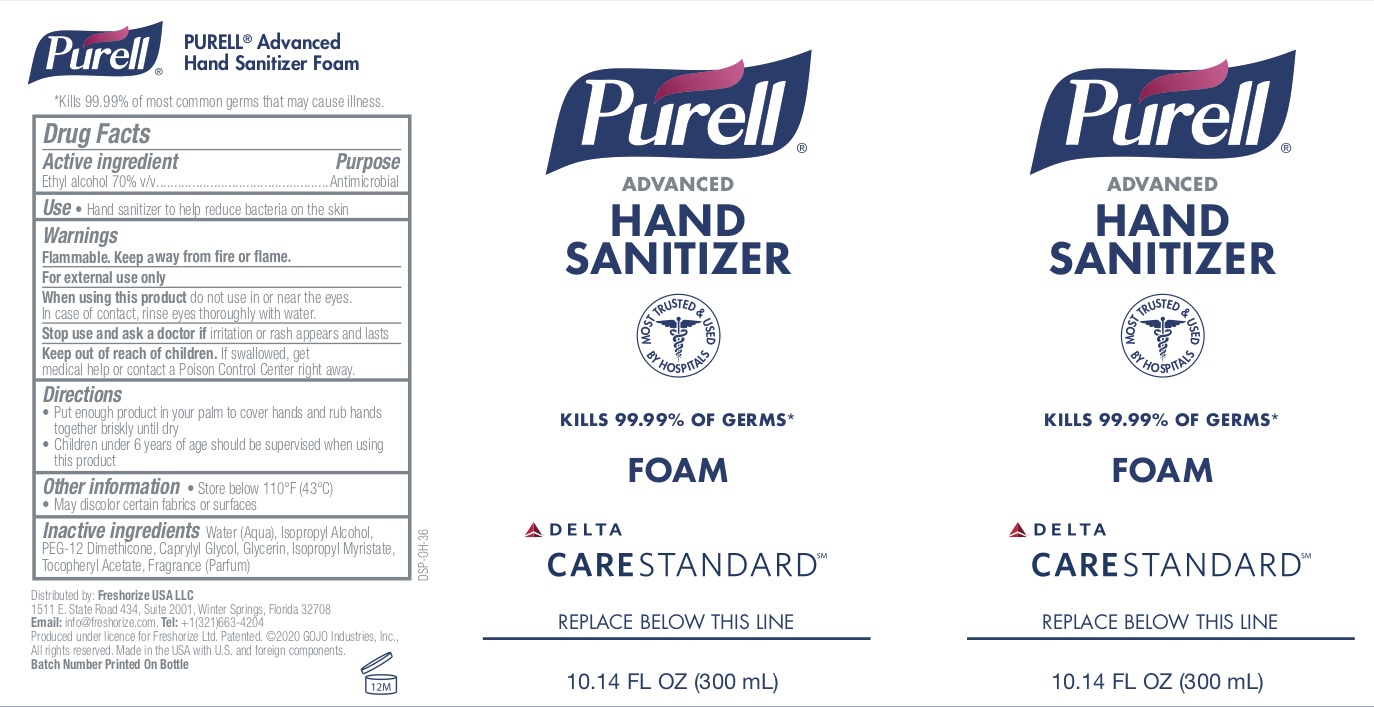 DRUG LABEL: Advanced
NDC: 52305-940 | Form: LIQUID
Manufacturer: Freshorize Ltd
Category: otc | Type: HUMAN OTC DRUG LABEL
Date: 20200824

ACTIVE INGREDIENTS: ALCOHOL 70 mL/100 mL
INACTIVE INGREDIENTS: ISOPROPYL ALCOHOL; .ALPHA.-TOCOPHEROL ACETATE; WATER; GLYCERIN; CAPRYLYL GLYCOL; ISOPROPYL MYRISTATE; PEG-12 DIMETHICONE (300 CST)

Hand Sanitizer

ACTIVE INGREDIENT

Ethyl Alcohol 70%

PURPOSE

Antimicrobial

INDICATIONS AND USAGE

Hand sanitizer to help reduce bacteria on the skin.

WARNINGS

Flammable-keep away from fire or flame. For external use only. When using this product do not use in or near the eyes. In case of contact, rinse eyes thoroughly with water. Stop use and ask a doctor if irritation or rash appears and lasts.

KEEP OUT OF REACH OF CHILDREN

If swallowed, get medical help or contact a Poison Control Center right away.

DOSAGE AND ADMINISTRATION

Wet hands thoroughly with product and allow to dry without wiping. For children under 6, use only under adult supervision. Not recommended for infants.

INACTIVE INGREDIENT

Water, Isopropyl Alcohol, Isopropyl Alcohol, PEG-12 Dimethicone, Caprylyl Glycol, Glycerin, Propylene Glycol, Isopropyl Myristate, Tocopheryl Acetate, Fragrance.